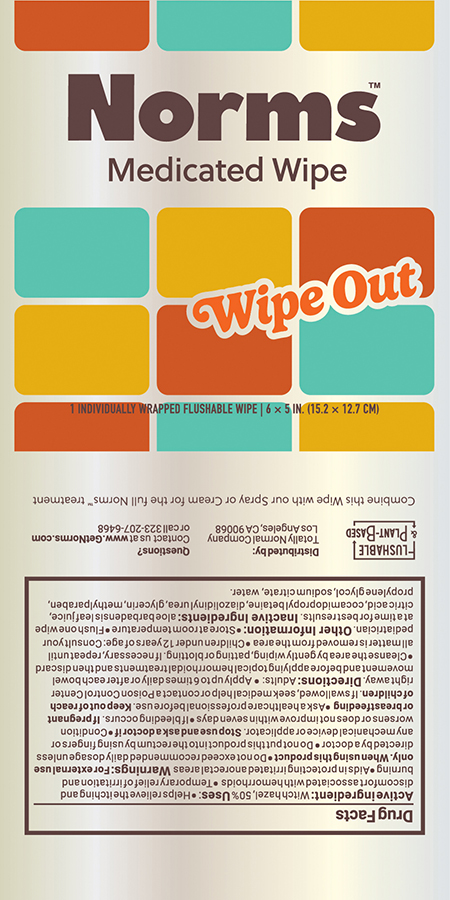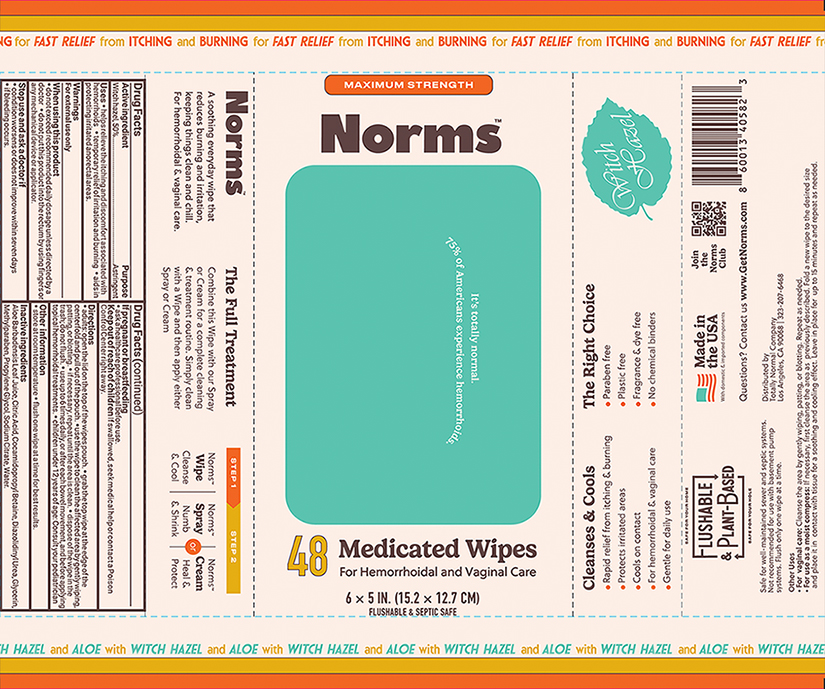 DRUG LABEL: Norms Medicated Wipes
NDC: 85996-001 | Form: CLOTH
Manufacturer: Totally Normal Company
Category: otc | Type: HUMAN OTC DRUG LABEL
Date: 20250826

ACTIVE INGREDIENTS: WITCH HAZEL 0.5 g/1 g
INACTIVE INGREDIENTS: COCAMIDOPROPYL BETAINE; DIAZOLIDINYL UREA; METHYLPARABEN; ALOE VERA LEAF; PROPYLENE GLYCOL; GLYCERIN; WATER; SODIUM CITRATE; CITRIC ACID MONOHYDRATE

Norms Medicated Wipe™

Active ingredient

Witch hazel, 50%

Purpose

Astringent

Uses

- helps relieve the itching and discomfort associated with hemorrhoids
- temporarily relief of irritation and burning
- aids in protecting irritated anorectal areas

Warnings

For external use only

- do not exceed the recommended daily dosage unless directed by a doctor
- do not put this product into the rectum by using fingers or any mechanical device or applicator

Stop use and ask a doctor if

- condition worsens or does not improve within 7 days
- bleeding occurs

If pregnant or breastfeeding ask a health professional before use.

Keep out of reach of children - If swallowed, seek medical help or contact Poison Control Center right away.

Directions

- Adults: open the lid on the top of the wipes pouch.
- Grab the top wipe at the edge of the centerfold and pull out of the pouch.
- Use the wipe to clean the affected area by gently wiping, patting, or blotting.
- If necessary, repeat until the area is clean. Dispose of the wipe in the trash; do not flush.
- Use up to 6 times daily, or after each bowel movement, and before applying topical hemorrhoidal treatments.
- Children under 12 years of age: Consult your pediatrician

Inactive ingredients

Aloe Barbadensis Leaf Juice, Citric Acid, Cocamidopropyl Betaine, Diazolidinyl Urea, Glycerin, Methylparaben, Propylene Glycol, Sodium Citrate, Water

Other information

- Store at room temperature
- Flush one wipe at the time for best results

PRINCIPAL DISPLAY PANEL

MAXIMUM STRENGTH
Norms™
It’s totally normal
75% of Americans experience hemorrhoids.
48 Medicated Wipes
For Hemorrhoid Wipes and Vaginal Care
6 x 5 IN. (15.2 x 12.7 CM)
FLUSHABLE & SEPTIC SAFE